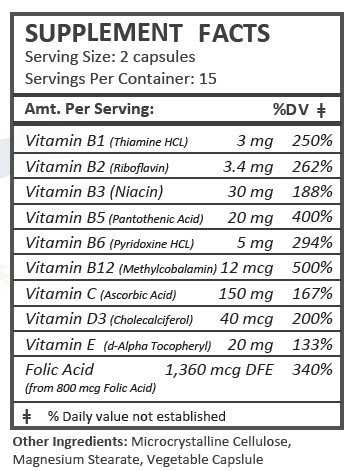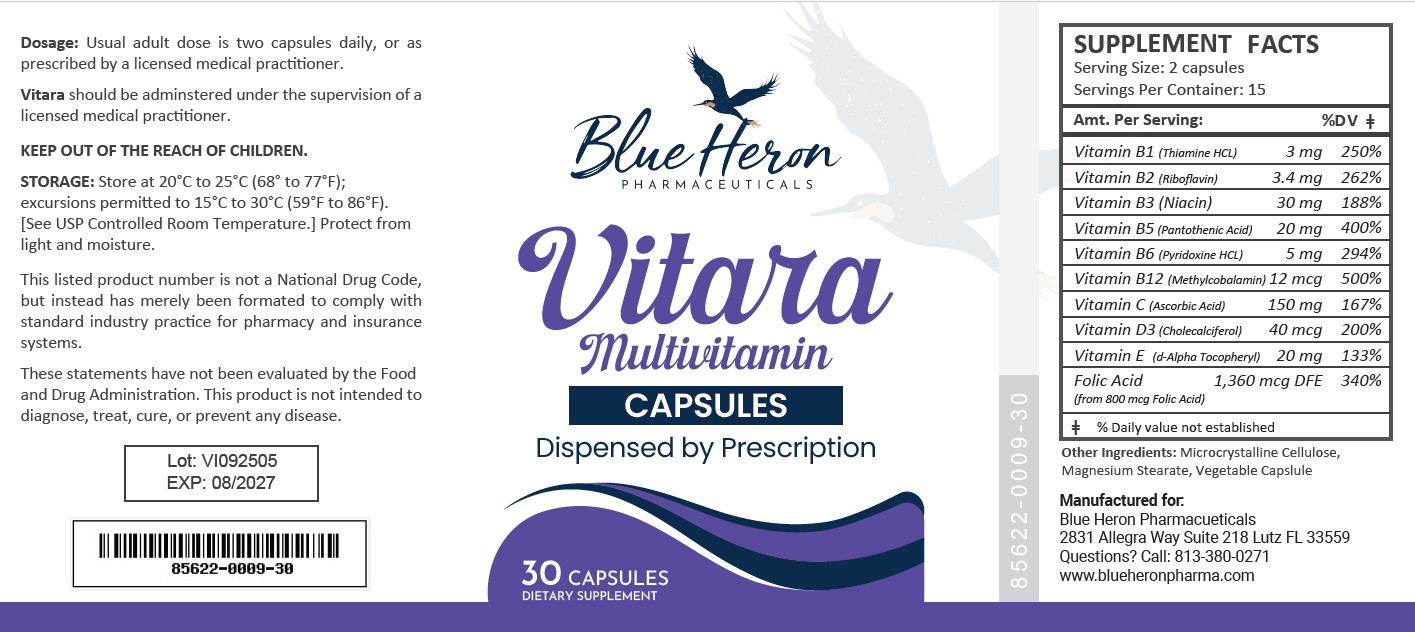 DRUG LABEL: Vitara
NDC: 85622-009 | Form: CAPSULE
Manufacturer: Blue Heron Pharmaceuticals, LLC
Category: other | Type: Dietary Supplement
Date: 20260213

ACTIVE INGREDIENTS: THIAMINE HCL 1.5 mg/1 1; RIBOFLAVIN 1.7 mg/1 1; NIACINAMIDE 15 mg/1 1; PANTOTHENIC ACID 10 mg/1 1; PYRIDOXINE HYDROCHLORIDE 2.5 mg/1 1; METHYLCOBALAMIN 6 ug/1 1; ASCORBIC ACID 75 mg/1 1; CHOLECALCIFEROL 20 ug/1 1; .ALPHA.-TOCOPHEROL SUCCINATE, D- 10 mg/1 1; FOLIC ACID 1360 ug/1 1
INACTIVE INGREDIENTS: MICROCRYSTALLINE CELLULOSE; MAGNESIUM STEARATE

Vitara

HEALTH CLAIM:

Vitara Multivitamin Capsules

Dispensed by Prescription

DESCRIPTION:

Vitara Multivitamin Capsules are clear capsules dispensed in plastic bottles of 30 ct.

85622-0009-30

Reserved for Professional Recommendation

Vitara Multivitamin Capsules are an orally administered prescription vitamin to provide significant amounts of Vitamins B6, B12, C, D3, E, riboflavin, niacinamide, thiamine monoitrate, and folate to supplement the diet, and to help assure that nutritional deficiencies of these vitamines will not develop.

Vitara Multivitamin Capsules should be administered under the supervision of a licensed medical practitioner.

This listed product is not a National Drug Code, but instead has merely been formatted to comply with standard industry practice for pharmacy and insurance computer systems.

These statements have not been evaluated by the Food and Drug Administration. This product is not intended to diagnose, treat, cure or prevent any disease.

All prescriptions using this product shall be pursuant to state statutes as applicable. This is not an Orange Book product. This product may be administered only under a physician’s supervision. There are no implied or explicit claims on therapeutic equivalence.

Manufactured for:

Blue Heron Pharmaceuticals

Lutz, FL 33559

WARNINGS:

This product is contraindicated in patients with a known hypersensitivity to any of the ingredients.

Vitara Multivitamin Capsules should only be used under the direction and supervision of a licensed medical practitioner. Use with caution in patients that may have a medical condition, are pregnant, lactating, trying to conceive, under the age of 18, or taking medications.

These statements have not been evaluated by the Food and Drug Administration. This product is not intended to diagnose, treat, cure, or prevent any disease.

DOSAGE:

Usual adult dose is 2 capsules by mouth daily once daily, or as prescribed by a licensed medical practitioner.

PRECAUTIONS:

CONTRAINDICATIONS
This product is contraindicated in patients with known hypersensitivity to any of the ingredients.

PRECAUTIONS
This product is contraindicated in patients with a known hypersensitivity to any of the ingredients.

ADVERSE REACTIONS
Allergic sensitizations have been reported following oral administration of folic acid. Consult your physician immediately if adverse side effects occur.

KEEP OUT OF THE REACH OF CHILDREN.

STORAGE:

Store at 20° to 25°C (68° to 77°F; excursions permitted to 15° to 30°C (59° to 86°F) [See USP Controlled Room Temperature].